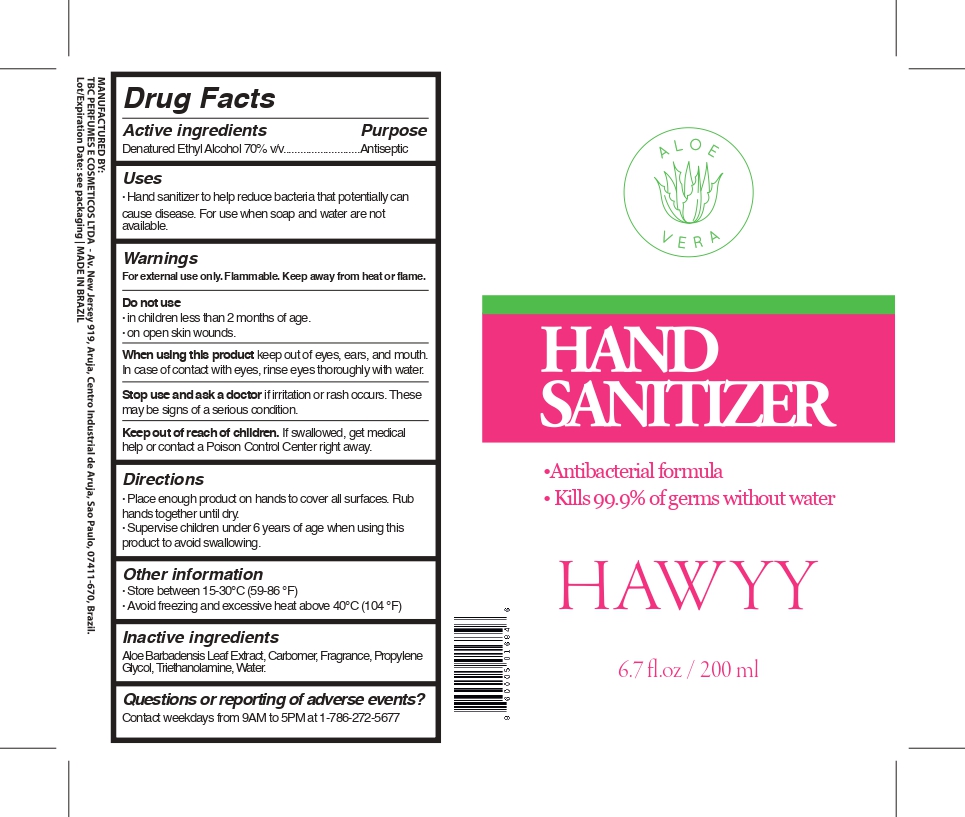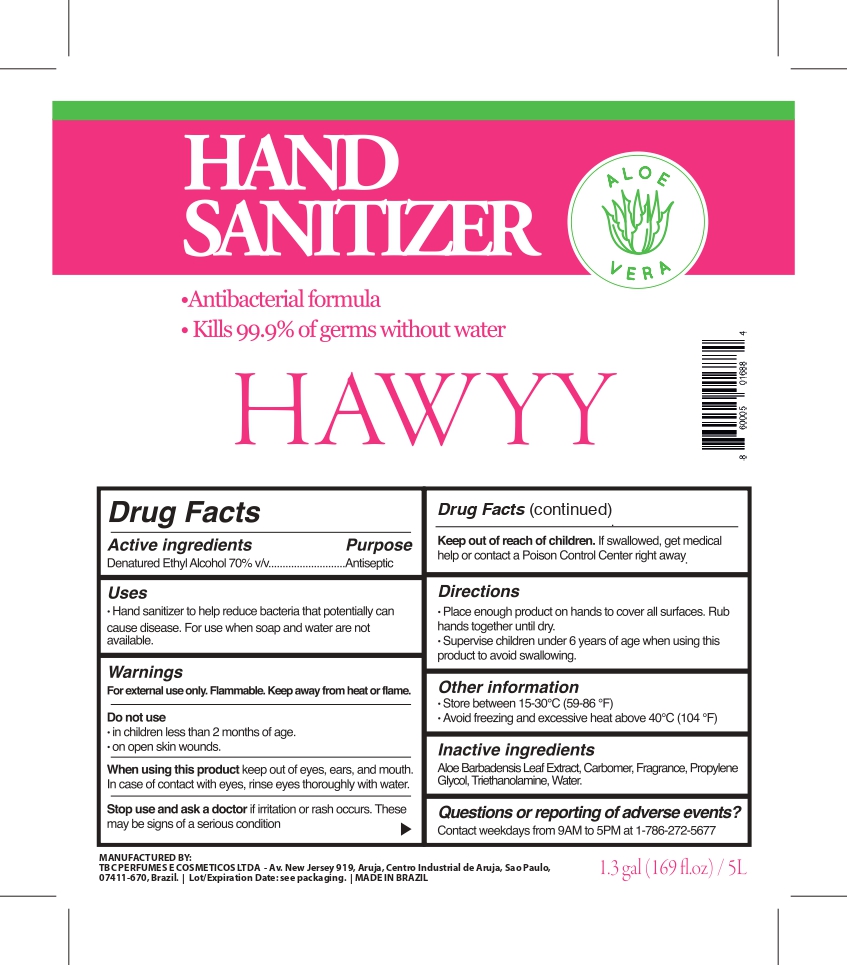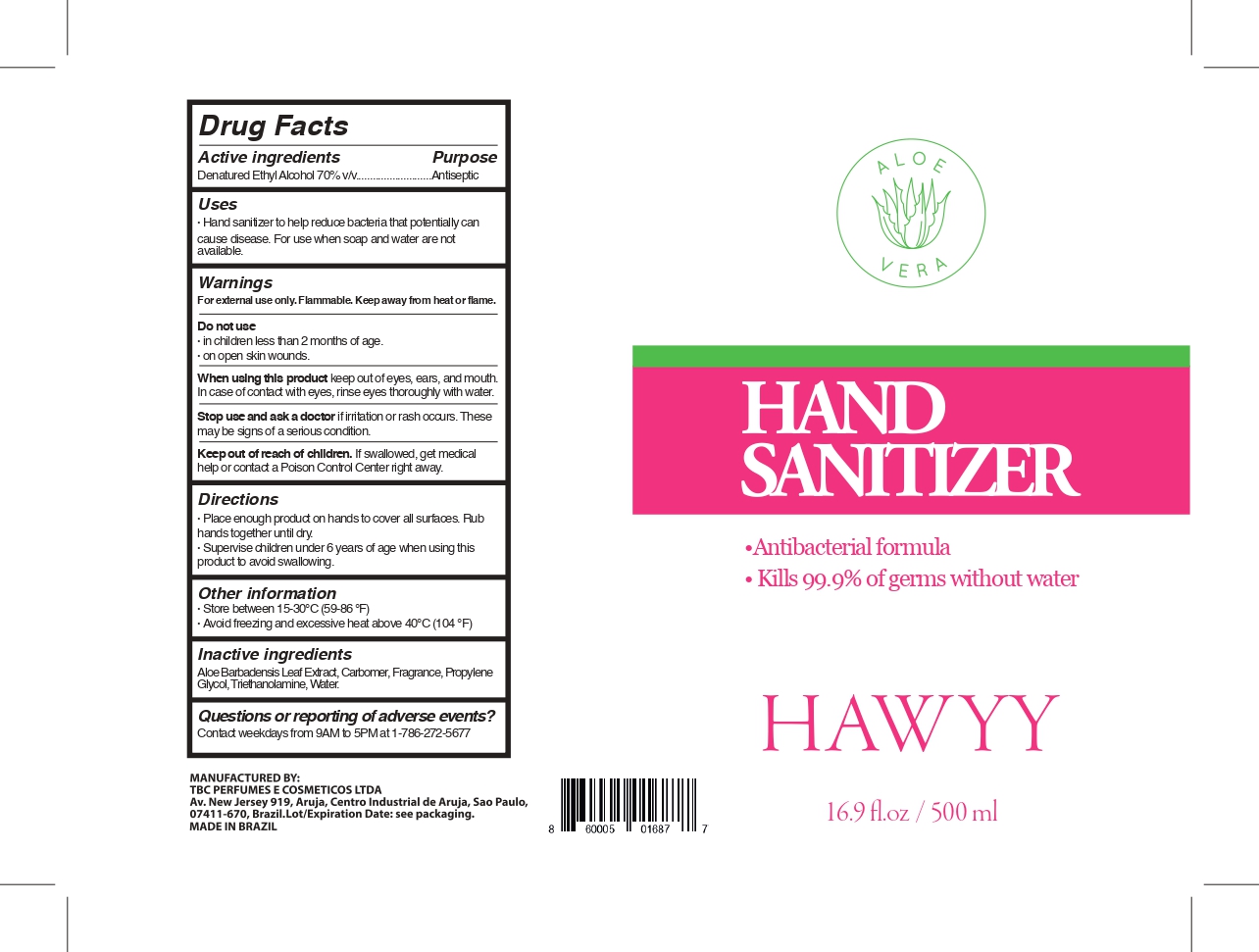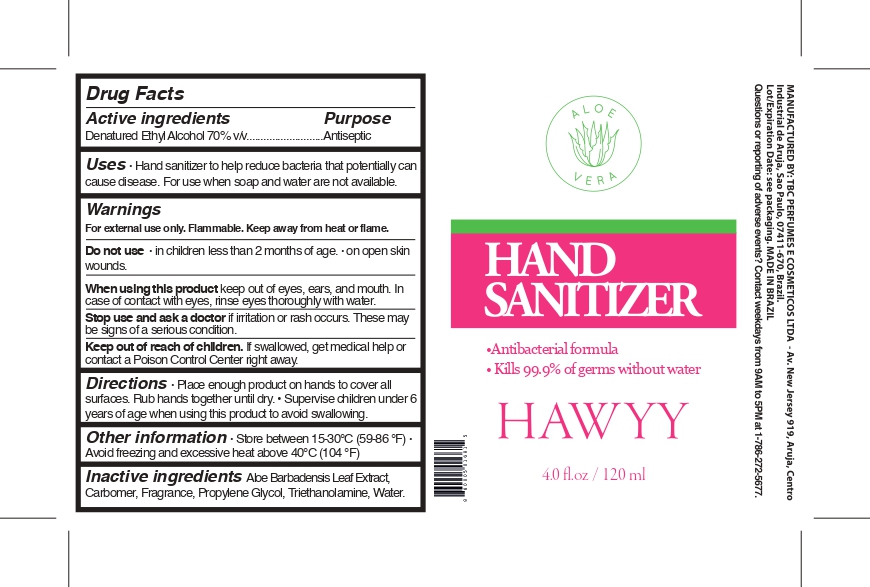 DRUG LABEL: Hawyy Hand Sanitizer
NDC: 78906-001 | Form: GEL
Manufacturer: TBC PERFUMES E COSMETICOS LTDA
Category: otc | Type: HUMAN OTC DRUG LABEL
Date: 20201207

ACTIVE INGREDIENTS: ALCOHOL 70 mL/100 mL
INACTIVE INGREDIENTS: CARBOMER HOMOPOLYMER TYPE B (ALLYL PENTAERYTHRITOL CROSSLINKED) 0.34 mL/100 mL; WATER 28.568 mL/100 mL; TROLAMINE 0.497 mL/100 mL; PROPYLENE GLYCOL 0.17 mL/100 mL; ALOE VERA LEAF 0.025 mL/100 mL

NO CHANGE NOTIFICATION

Drug Facts Panel - Active Ingredients

Denatured Ethyl Alcohol 70% v/v. Purpose: Antiseptic

Drug Facts Panel - Purpose

Purpose: Antiseptic.

Drug Facts Panel - Use

Use: Hand sanitizer to help reduce bacteria that potentially can cause disease. For use when soap and water are not available.

Drug Facts Panel - Warnings

For external use only. Flammable. Keep away from heat or flame.
Do not use
● in children less than 2 months of age
● on open skin wounds
When using this product keep out of eyes, ears, and mouth. In case of contact with eyes, rinse eyes thoroughly with water.
Stop use and ask a doctor if irritation or rash occurs. These may be signs of a serious condition.
Keep out of reach of children. If swallowed, get medical help or contact a Poison Control Center right away.

Do not use
● in children less than 2 months of age
● on open skin wounds

When using this product keep out of eyes, ears, and mouth. In case of contact with eyes, rinse eyes thoroughly with water.

Stop use and ask a doctor if irritation or rash occurs. These may be signs of a serious condition.

Keep out of reach of children. If swallowed, get medical help or contact a Poison Control Center right away.

Drug Facts Panel - Directions

Place enough product on hands to cover all surfaces. Rub hands together until dry.
Supervise children under 6 years of age when using this product to avoid swallowing.

Drug Facts Panel - Other Information

Store between 15-30 °C (59-86 °F)
Avoid freezing and excessive heat above 40 °C (104 °F)

Drug Facts Panel - Inactive Ingredients

Aloe Barbadensis Leaf Extract, Carbomer, Fragrance, Propylene Glycol, Triethanolamine, Water.

Package Label - Principal Display Panel

120 ml, NDC 78906-001-01

200 ml, NDC 78906-001-02

500 ml, bottle NDC 78906-001-03

500 ml, pump NDC 78906-001-04

5000 ml NDC 78906-001-05